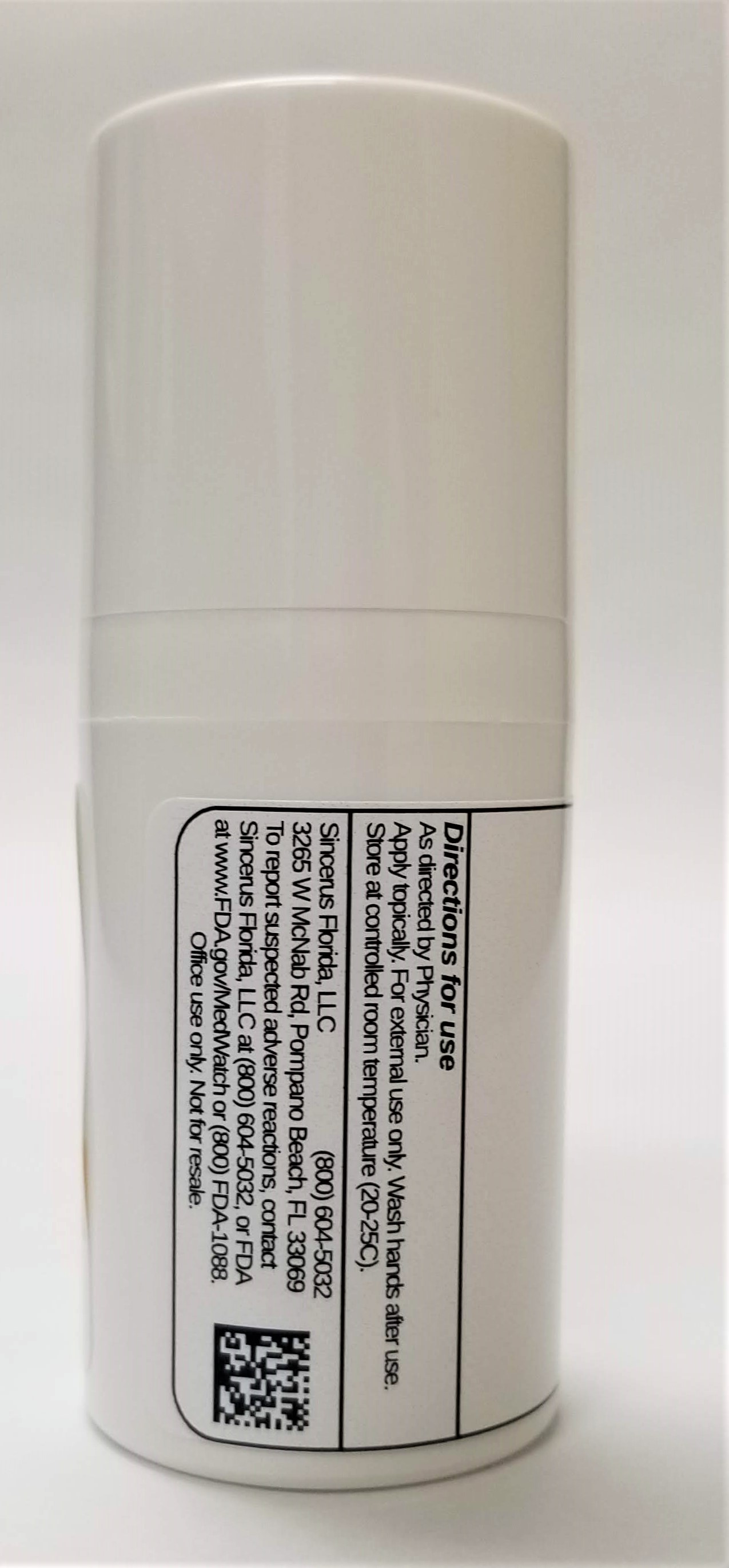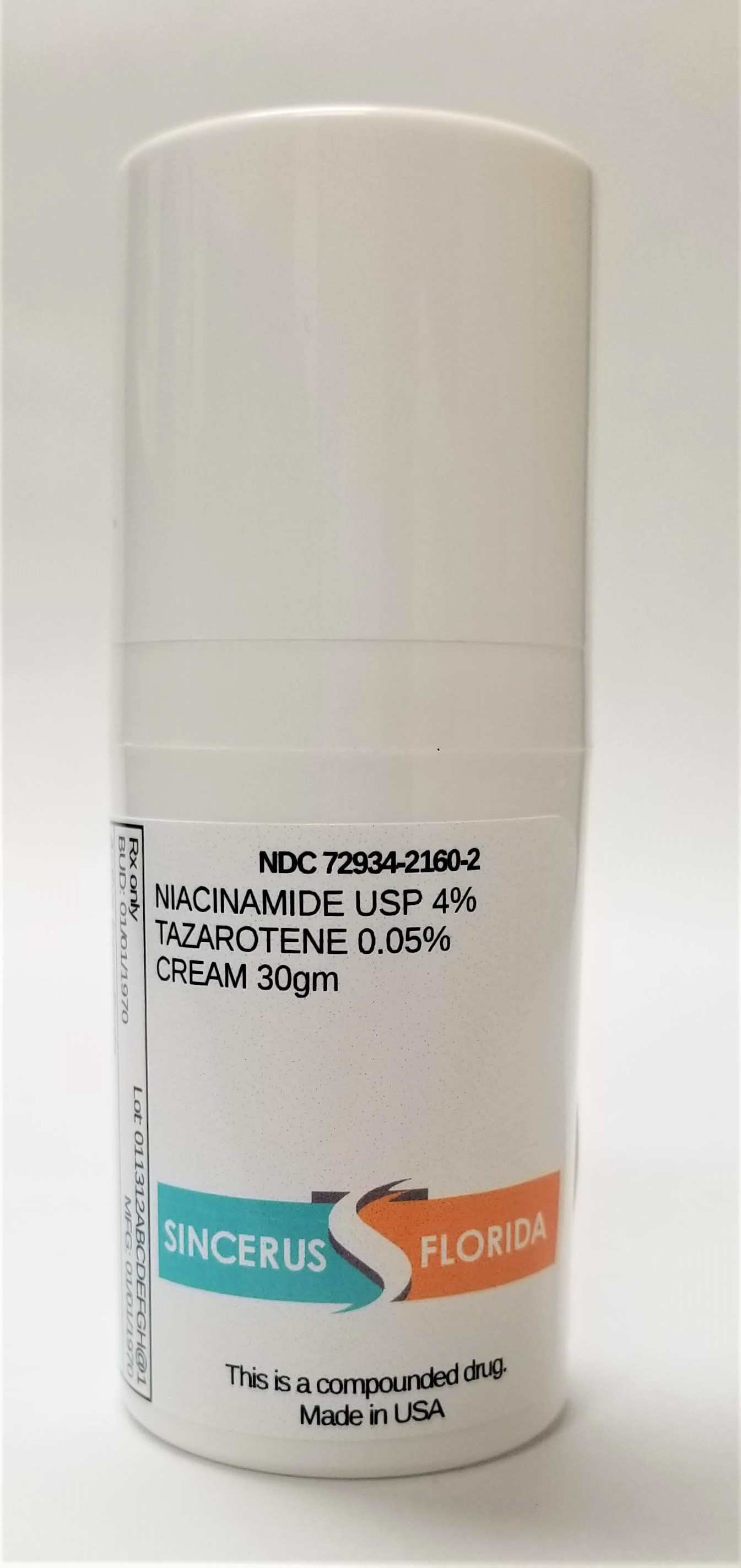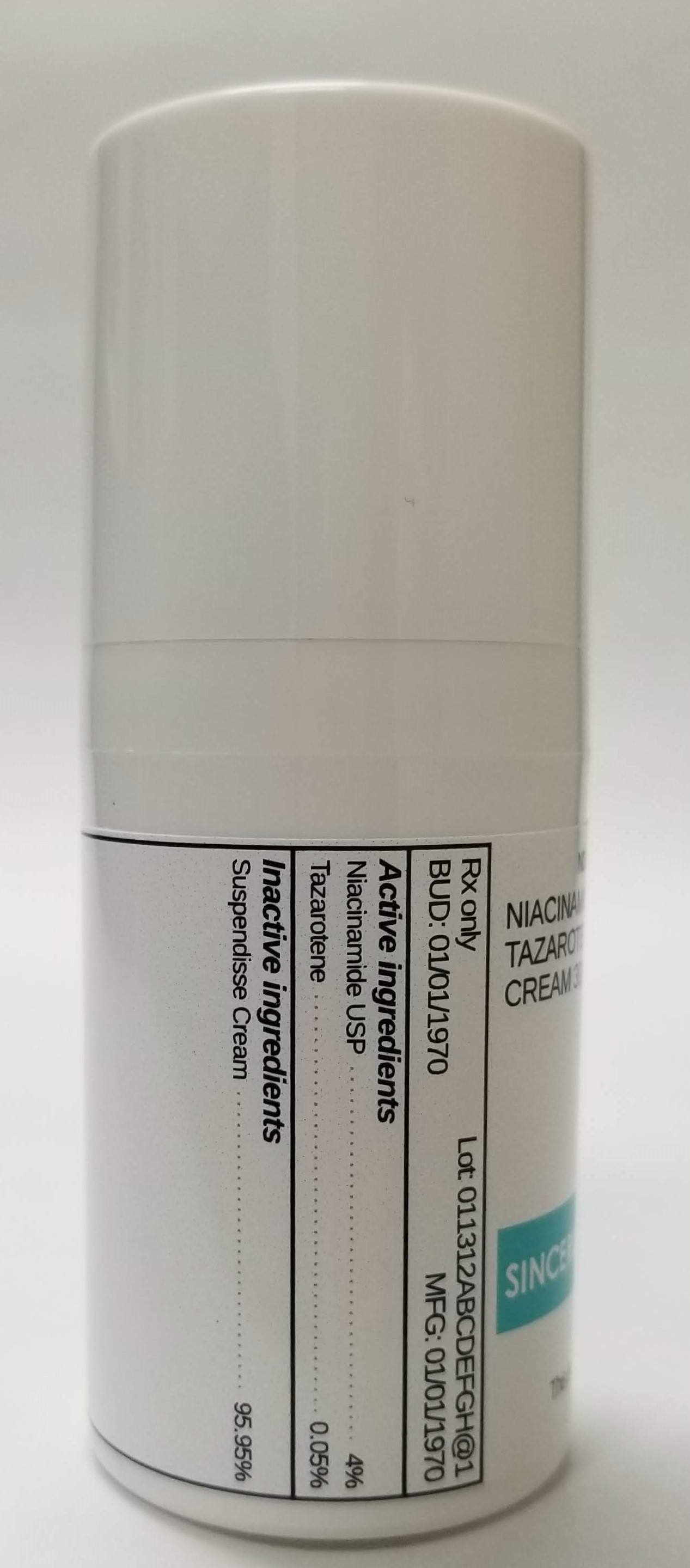 DRUG LABEL: NIACINAMIDE 4% / TAZAROTENE 0.05%
NDC: 72934-2160 | Form: CREAM
Manufacturer: Sincerus Florida, LLC
Category: prescription | Type: HUMAN PRESCRIPTION DRUG LABEL
Date: 20190423

ACTIVE INGREDIENTS: NIACINAMIDE 4 g/100 g; TAZAROTENE 0.05 g/100 g

NIACINAMIDE 4% / TAZAROTENE 0.05%